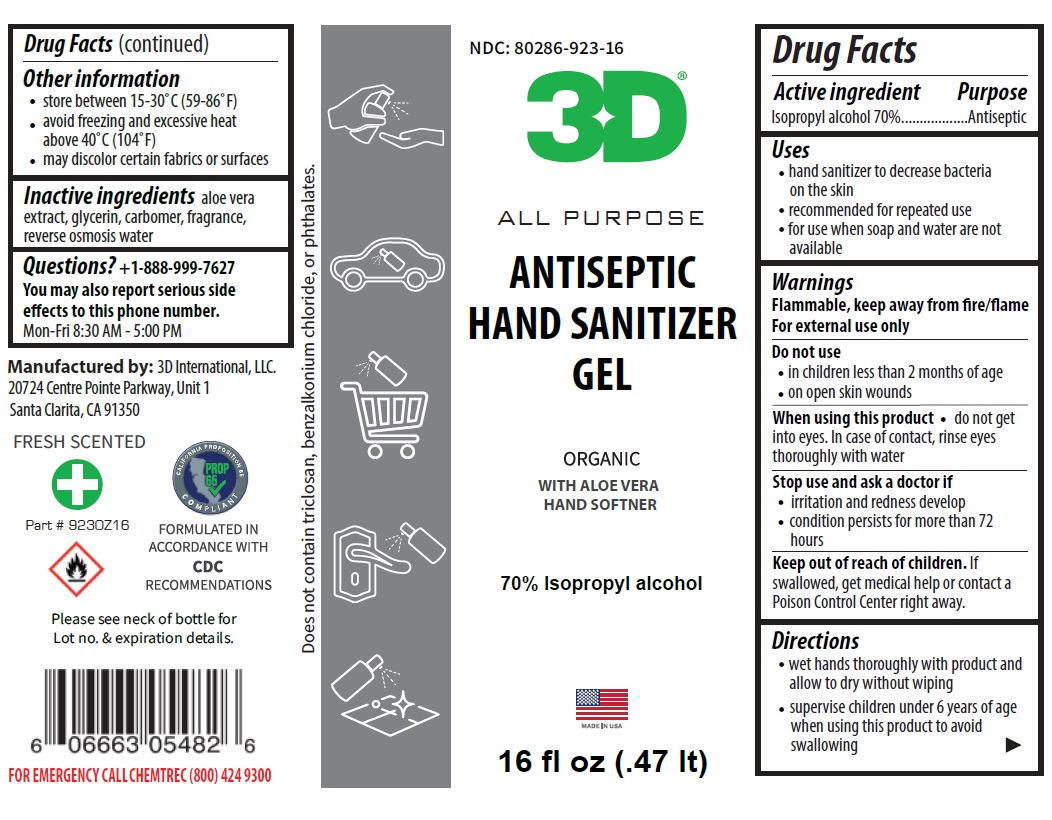 DRUG LABEL: 3D ANTISEPTIC HAND SANITIZER
NDC: 80286-923 | Form: GEL
Manufacturer: 3d International Llc
Category: otc | Type: HUMAN OTC DRUG LABEL
Date: 20200911

ACTIVE INGREDIENTS: ISOPROPYL ALCOHOL 70 L/100 L
INACTIVE INGREDIENTS: ALOE VERA LEAF; GLYCERIN; CARBOMER HOMOPOLYMER, UNSPECIFIED TYPE; WATER

3D ANTISEPTIC HAND SANITIZER GEL

Active ingredient

Isopropyl alcohol 70%

Purpose

Antiseptic

Uses

- hand sanitizer to decrease bacteria on the skin
- recommended for repeated use
- for use when soap and water are not available

Warnings

Flammable, keep away from fire/flame

For external use only

Do not use

- in children less than 2 months of age
- on open skin wounds

When using this product • do not get into eyes. In case of contact, rinse eyes thoroughly with water

Stop use and ask a doctor if

- irritation and redness develop
- condition persists for more than 72hours

Keep out of reach of children. If swallowed, get medical help or contact a Poison Control Center right away.

Directions

- wet hands thoroughly with product and allow to dry without wiping
- supervise children under 6 years of age when using this product to avoid swallowing

Other information

- store between 15-30°C (59-86°F)
- avoid freezing and excessive heat above 40°C (104°F)
- may discolor certain fabrics or surfaces

Inactive ingredients

aloe vera extract, glycerin, carbomer, fragrance, reverse osmosis water

Questions?

+1-888-999-7627

You may also report serious side effects to this number. Mon-Fri 8:30 AM - 5:00 PM

ALL PURPOSE

ORGANIC

WITH ALOE VERA HAND SOFTNER

TSA APPROVED SIZE

MADE IN USA

Manufactured by: 3D International, LLC.
20724 Centre Pointe Parkway,Unit 1
Santa Clarita, CA 91350

FRESH SCENTED

CALIFORNIA PROPOSITION

PROP 65

FORMULATED IN ACCORDANCE WITH CDC RECOMMENDATIONS

Does not contain triclosan, benzalkonium chloride, or phthalates

FOR EMERGENCY CALLCHEMTREC (800) 424 9300